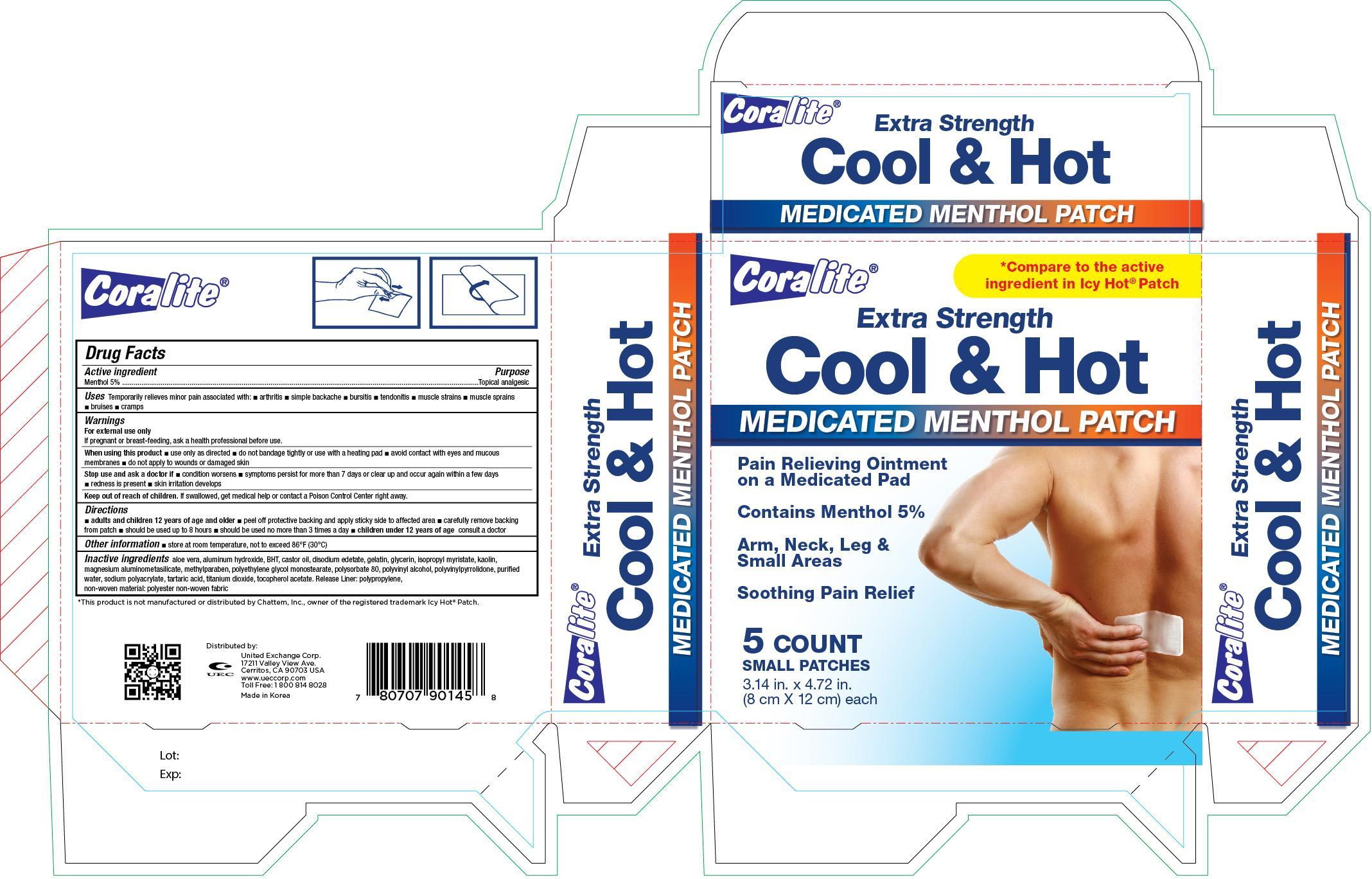 DRUG LABEL: Coralite Extra Strength Cool and Hot
NDC: 65923-145 | Form: PATCH
Manufacturer: United Exchange Corp.
Category: otc | Type: HUMAN OTC DRUG LABEL
Date: 20141231

ACTIVE INGREDIENTS: MENTHOL 50 mg/1 g
INACTIVE INGREDIENTS: ALOE VERA LEAF; ALUMINUM HYDROXIDE; CASTOR OIL; GELATIN; GLYCERIN; ISOPROPYL MYRISTATE; KAOLIN; MAGNESIUM ALUMINUM SILICATE; METHYLPARABEN; POLYSORBATE 80; POLYVINYL ALCOHOL; WATER; SODIUM POLYACRYLATE (8000 MW); TARTARIC ACID; TITANIUM DIOXIDE

Active ingredient Purpose

Menthol 5%........................................................................... Topical analgesic

Uses

Temporarily relieves minor pain associated with:

- arthritis
- simple backache
- bursitis
- tendonitis
- muscle strains
- muscle sprains
- bruises
- cramps

Warnings

For external use only

PREGNANCY OR BREAST FEEDING

If pregnant or breast-feeding, ask a health professional before use

When using this product

- use only as directed
- do not bandage tightly or use with a heating pad
- avoid contact with eyes and mucous membranes
- do not apply to wounds or damaged skin

Keep out of reach of children

If swallowed, get medical help or contact a Poison Control Center right away

Directions

- adults and children 12 years of age and older
- peel off protective backing and apply sticky side to affected area
- carefully remove backing from patch
- should be used up to 8 hours
- should be used no more than 3 times a day
- children 12 years of age consult a doctor

Other information

- store at room temperature, not to exceed 86°F (30°C)

Inactive ingredients

aloe vera, aluminum hydroxide, BHT, castor oil, disodium edetate, gelatin, glycerin, isopropyl myristate, kaolin, magnesium aluminometasilicate, methylparaben, polyethylene glycol monostearate, polysorbate 80, polyvinyl alcohol, polyvinylpyrrolidone, purified water, sodium polyacrylate, tartaric acid, titanium dioxide, tocopherol acetate, Release Liner: polypropylene, non-woven material: polyester non-woven fabric

DOSAGE AND ADMINISTRATION

DISTRIBUTED BY:

UNITED EXCHANGE CORP.

17211 VALLEY VIEW AVE.

CERRITOS, CA 90703 USA

MADE IN KOREA